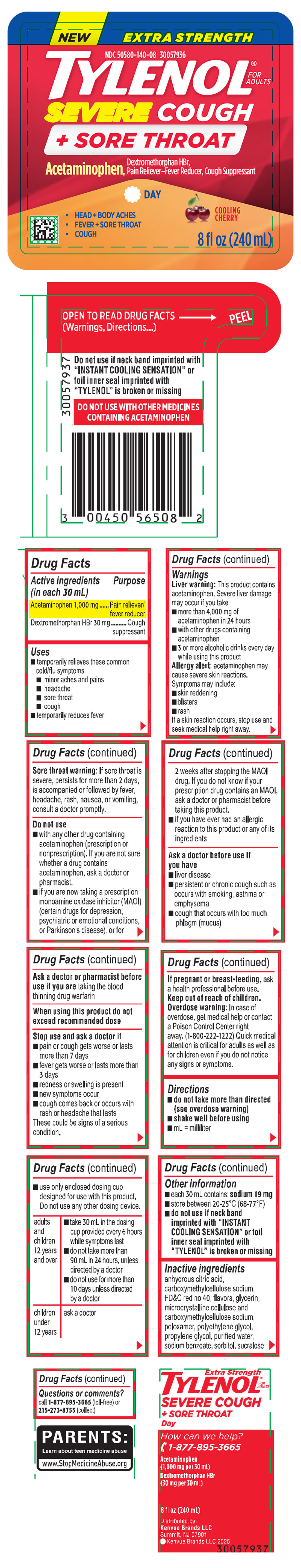 DRUG LABEL: Extra Strength TYLENOL Severe Cough Plus Sore Throat Day
NDC: 50580-140 | Form: LIQUID
Manufacturer: Kenvue Brands LLC
Category: otc | Type: HUMAN OTC DRUG LABEL
Date: 20250307

ACTIVE INGREDIENTS: ACETAMINOPHEN 1000 mg/30 mL; DEXTROMETHORPHAN HYDROBROMIDE 30 mg/30 mL
INACTIVE INGREDIENTS: WATER; CARBOXYMETHYLCELLULOSE SODIUM, UNSPECIFIED; FD&C RED NO. 40; MICROCRYSTALLINE CELLULOSE; POLYETHYLENE GLYCOL, UNSPECIFIED; SODIUM BENZOATE; SUCRALOSE; PROPYLENE GLYCOL; GLYCERIN; ANHYDROUS CITRIC ACID; SORBITOL

Extra Strength TYLENOL® Severe Cough + Sore Throat Day

Drug Facts

Active ingredients(in each 30 mL)

Acetaminophen 1,000 mg

Dextromethorphan HBr 30 mg

Purpose

Pain reliever/fever reducer

Cough suppressant

Uses

- temporarily relieves these common cold/flu symptoms:
- minor aches and pains
- headache
- sore throat
- cough
- temporarily reduces fever

Warnings

Liver Warning

This product contains acetaminophen. Severe liver damage may occur if you take

- more than 4,000 mg of acetaminophen in 24 hours
- with other drugs containing acetaminophen
- 3 or more alcoholic drinks every day while using this product

Allergy alert

acetaminophen may cause severe skin reactions.

Symptoms may include:

- skin reddening
- blisters
- rash

If a skin reaction occurs, stop use and seek medical help right away.

Sore throat warning

If sore throat is severe, persists for more than 2 days, is accompanied or followed by fever, headache, rash, nausea, or vomiting,
consult a doctor promptly.

Do not use

- with any other drug containing acetaminophen (prescription or nonprescription). If you are not sure whether a drug contains

acetaminophen, ask a doctor or pharmacist.

- if you are now taking a prescription monoamine oxidase inhibitor (MAOI) (certain drugs for depression psychiatric or emotional conditions, or Parkinson’s disease), or for 2 weeks after stopping the MAOI drug. If you do not know if your prescription drug contains an MAOI,ask a doctor or pharmacist before taking this product.
- if you have ever had an allergic reaction to this product or any of its ingredients

Ask a doctor before use if you have

- liver disease
- persistent or chronic cough such as occurs with smoking, asthma or emphysema
- cough that occurs with too much phlegm (mucus)

Ask a doctor or pharmacist before use if you are

taking the blood thinning drug warfarin

When using this product

do not exceed recommended dose

Stop use and ask a doctor if

- pain or cough gets worse or lasts more than 7 days
- fever gets worse or lasts more than 3 days
- redness or swelling is present
- new symptoms occur
- cough comes back or occurs with rash or headache that lasts

These could be signs of a serious condition.

If pregnant or breast-feeding, ask a health professional before use.

Keep out of reach of children.

Overdose warning

In case of overdose, get medical help or contact a Poison Control Center right away. (1-800-222-1222) Quick medical
attention is critical for adults as well as for children even if you do not notice any signs or symptoms.

Directions

- do not take more than directed(see overdose warning)
- shake well before using
- mL = milliliter
- use only enclosed dosing cup designed for use with this product. Do not use any other dosing device.

adults and children 12 years and over | - take 30 mL in the dosing cup provided every 6 hours while symptoms last - do not take more than 90 mL in 24 hours, unless directed by a doctor - do not use for more than 10 days unless directed by a doctor
children under 12 years | ask a doctor

Other information

- each 30 mL contains: sodium 19 mg
- store between 20-25°C (68-77°F)
- do not use if neck band imprinted with “INSTANT COOLING SENSATION” or foil inner seal imprinted with

“TYLENOL” is broken or missing

Inactive ingredients

anhydrous citric acid, carboxymethylcellulose sodium, FD&C red no 40, flavors, glycerin,microcrystalline cellulose and carboxymethylcellulose sodium,poloxamer, polyethylene glycol,propylene glycol, purified water,sodium benzoate, sorbitol, sucralose

Questions or comments?

call 1-877-895-3665 (toll-free) or

215-273-8755 (collect)

PRINICIPAL DISPLAY PANEL

NEW

NDC 50580-140-08

EXTRA STRENGHT TYLENOL®

FOR ADULTS

SEVERE COUGH + SORE THROAT

Acetaminophen,

Dextromethorphan HBr, Pain Reliever-Fever Reducer, Cough Suppressant

- HEAD+BODY ACHES
- FEVER+ SORE THROAT
- COUGH

DAY

COOLING CHERRY

8 fl oz (240 mL)